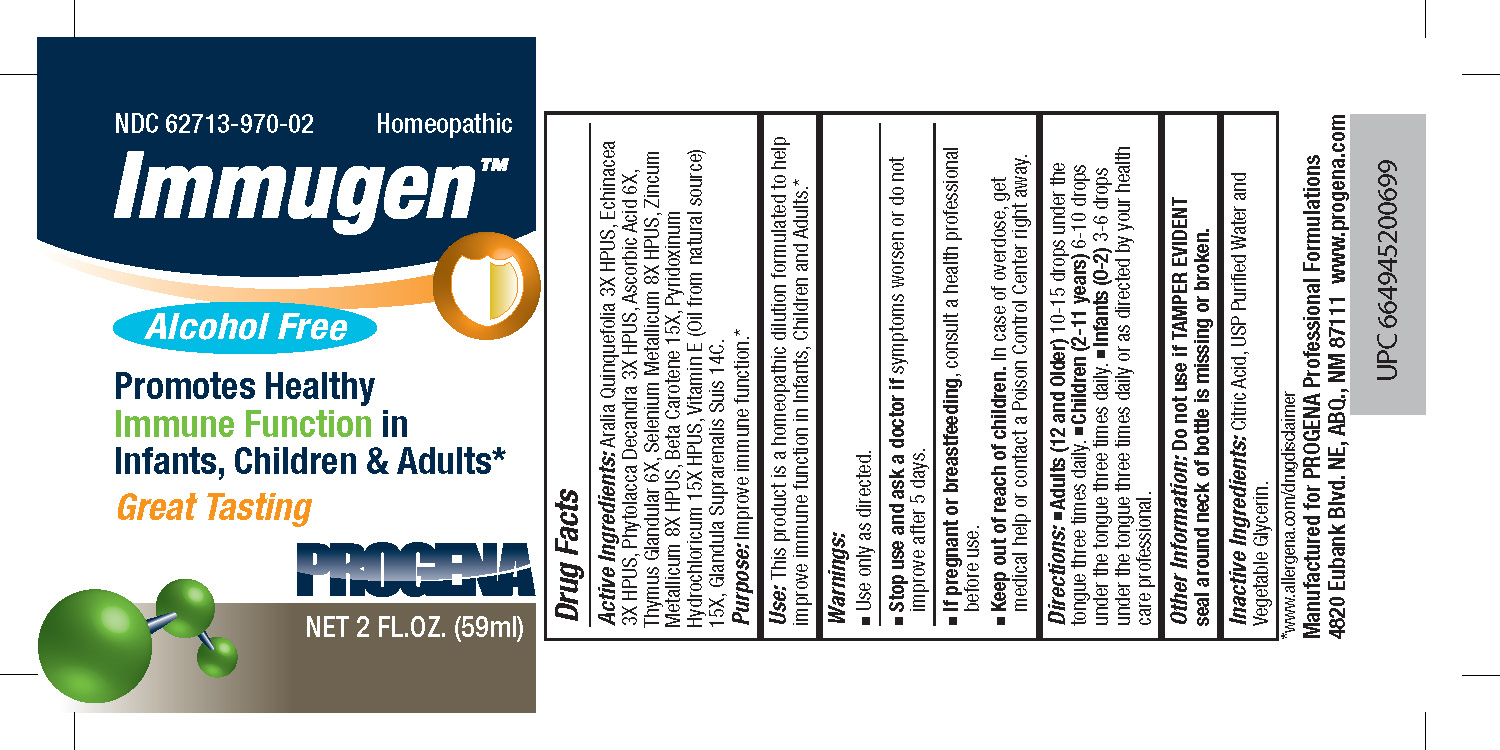 DRUG LABEL: Progena Immugen
NDC: 62713-970 | Form: LIQUID
Manufacturer: Meditrend, Inc. DBA Progena Professional Formulations
Category: homeopathic | Type: HUMAN OTC DRUG LABEL
Date: 20250129

ACTIVE INGREDIENTS: AMERICAN GINSENG 3 [hp_X]/1 mL; ECHINACEA, UNSPECIFIED 3 [hp_X]/1 mL; PHYTOLACCA AMERICANA ROOT 3 [hp_X]/1 mL; ASCORBIC ACID 6 [hp_X]/1 mL; .BETA.-CAROTENE 15 [hp_X]/1 mL; SUS SCROFA ADRENAL GLAND 6 [hp_X]/1 mL; PYRIDOXINE HYDROCHLORIDE 15 [hp_X]/1 mL; SUS SCROFA SPLEEN 6 [hp_X]/1 mL; SUS SCROFA THYMUS 6 [hp_X]/1 mL; SELENIUM 8 [hp_X]/1 mL; .ALPHA.-TOCOPHEROL 15 [hp_X]/1 mL; ZINC 8 [hp_X]/1 mL
INACTIVE INGREDIENTS: CITRIC ACID MONOHYDRATE; WATER; GLYCERIN

Progena Immugen

ACTIVE INGREDIENT

Active Ingredients:Aralia Quinquefolia 3X HPUS, Echinacea 3X HPUS, Phytolacca Decandra 3X HPUS, Ascorbic Acid 6X, Thymus Glandular 6X, Selenium Metallicum 8X HPUS, Zincum Metallicum 8X HPUS, Beta Carotene 15X, Pyridoxinum Hydrochloricum 15X HPUS, Vitamin E (Oil from natural source) 15X, Glandula Suprarenalis 10C.

Purpose:Improve immune function.*

INDICATIONS AND USAGE

Use:This product is a Homeopathic Dilution formulated to help improve immune function in Infants, Children and Adults.*

Keep Out of Reach of Children.In case of overdose, get medical help or contact a Poison Control Center right away.

Warnings:

- Use Only as directed.
- Stop use and ask a doctor ifsymptoms worsen or do not improve after 5 days.
- If pregnant or breast-feeding, consult a health professional before use.

DOSAGE AND ADMINISTRATION

Directions:• Adults (12 and Older)10-15 drops under the tongue three times daily.• Children (2-11 years)6-10 drops under the tongue three times daily.• Infants (1-2)3-6 drops under the tongue three times daily or as directed by your health care professional.

Other Information: Do not use if TAMPER EVIDENT seal around neck of bottle is missing or broken.

INACTIVE INGREDIENT

Inactive Ingredients:Citric Acid, USP Purified Water and Vegetable Glycerin.

PACKAGE LABEL

*www.allergena.com/drugdisclaimer
Manufactured for PROGENA Professional Formulations
4820 Eubank Blvd. NE, ABQ, NM 87111, www.progena.com